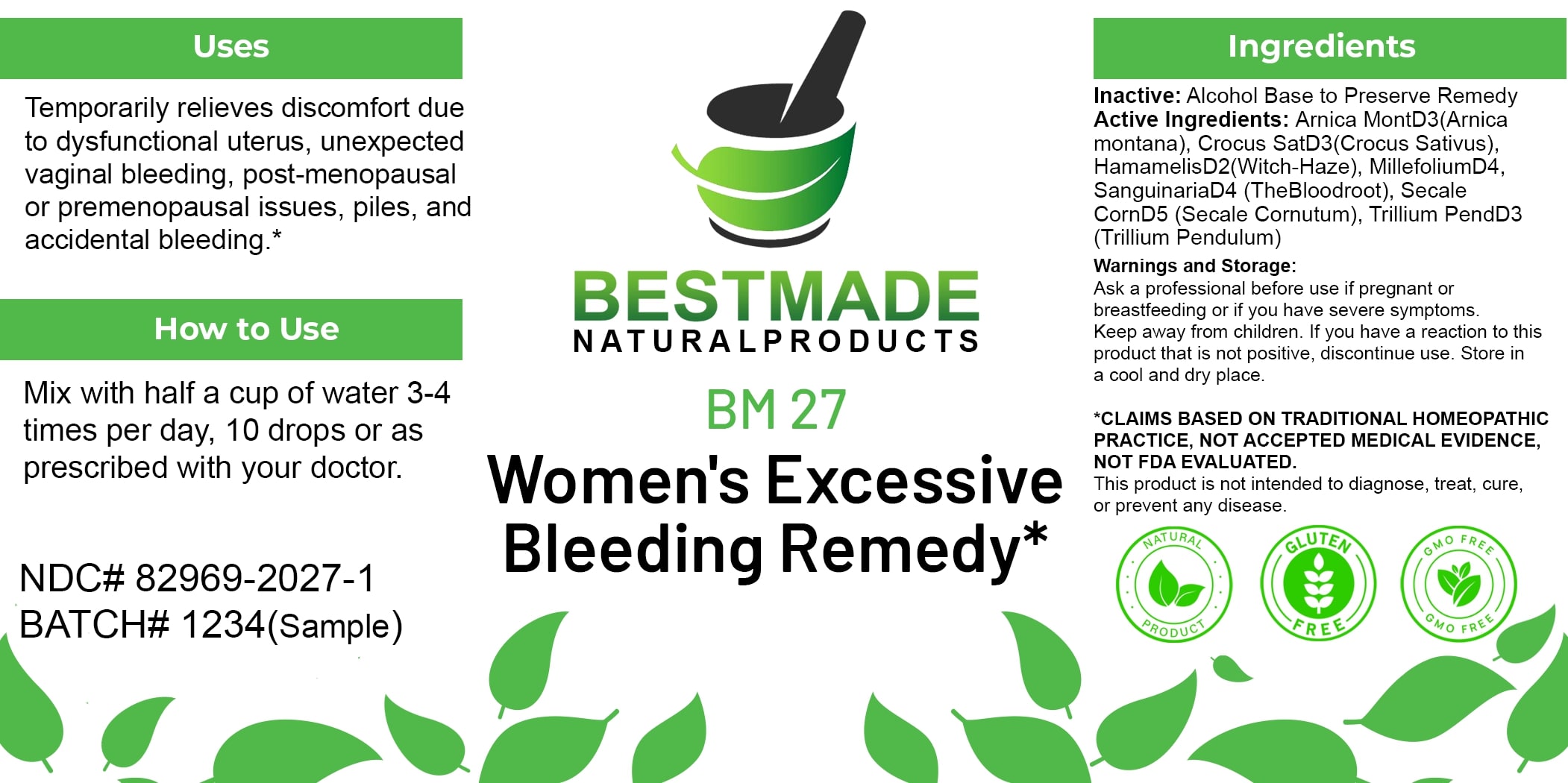 DRUG LABEL: Bestmade Natural Products BM27
NDC: 82969-2027 | Form: LIQUID
Manufacturer: Bestmade Natural Products
Category: homeopathic | Type: HUMAN OTC DRUG LABEL
Date: 20250123

ACTIVE INGREDIENTS: CLAVICEPS PURPUREA SCLEROTIUM 30 [hp_C]/30 [hp_C]; TRILLIUM ERECTUM ROOT 30 [hp_C]/30 [hp_C]; SANGUINARIA CANADENSIS ROOT 30 [hp_C]/30 [hp_C]; ARNICA MONTANA 30 [hp_C]/30 [hp_C]; SAFFRON 30 [hp_C]/30 [hp_C]; HAMAMELIS VIRGINIANA ROOT BARK/STEM BARK 30 [hp_C]/30 [hp_C]; ACHILLEA MILLEFOLIUM FLOWERING TOP 30 [hp_C]/30 [hp_C]
INACTIVE INGREDIENTS: ALCOHOL 30 [hp_C]/30 [hp_C]

BM27

DOSAGE AND ADMINISTRATION

How to Use

Mix with half a cup of water 3-4 times per day, 10 drops or as prescribed with your doctor.

INACTIVE INGREDIENT

Ingredients

Inactive: Alcohol Base to Preserve Remedy

Uses

Temporarily relieves discomfort due to dysfunctional uterus, unexpected vaginal bleeding, post-menopausal or premenopausal issues, piles, and accidental bleeding.*

*CLAIMS BASED ON TRADITIONAL HOMEOPATHIC PRACTICE, NOT ACCEPTED MEDICAL EVIDENCE, NOT FDA EVALUATED.

This product is not intended to diagnose, treat, cure, or prevent any disease.

Active Ingredients:

Arnica MontD3(Arnica montana), Crocus SatD3(Crocus Sativus), HamamelisD2(Witch-Hazel), MillefoliumD4, SanguinariaD4 (TheBloodroot), Secale CornD5 (Secale Cornutum), Trillium PendD3 (Trillium Pendulum)

Uses

Temporarily relieves discomfort due to dysfunctional uterus, unexpected vaginal bleeding, post-menopausal or premenopausal issues, piles, and accidental bleeding.*

*CLAIMS BASED ON TRADITIONAL HOMEOPATHIC PRACTICE, NOT ACCEPTED MEDICAL EVIDENCE, NOT FDA EVALUATED.

This product is not intended to diagnose, treat, cure, or prevent any disease.

KEEP OUT OF REACH OF CHILDREN

Warnings and Storage:

Ask a professional before use if pregnant or breastfeeding or if you have severe symptoms. Keep away from children. If you have a reaction to this product that is not positive, discontinue use. Store in a cool and dry place.

Warnings and Storage:

Ask a professional before use if pregnant or breastfeeding or if you have severe symptoms. Keep away from children. If you have a reaction to this product that is not positive, discontinue use. Store in a cool and dry place.

*CLAIMS BASED ON TRADITIONAL HOMEOPATHIC PRACTICE, NOT ACCEPTED MEDICAL EVIDENCE, NOT FDA EVALUATED.

This product is not intended to diagnose, treat, cure, or prevent any disease.

Entire package label